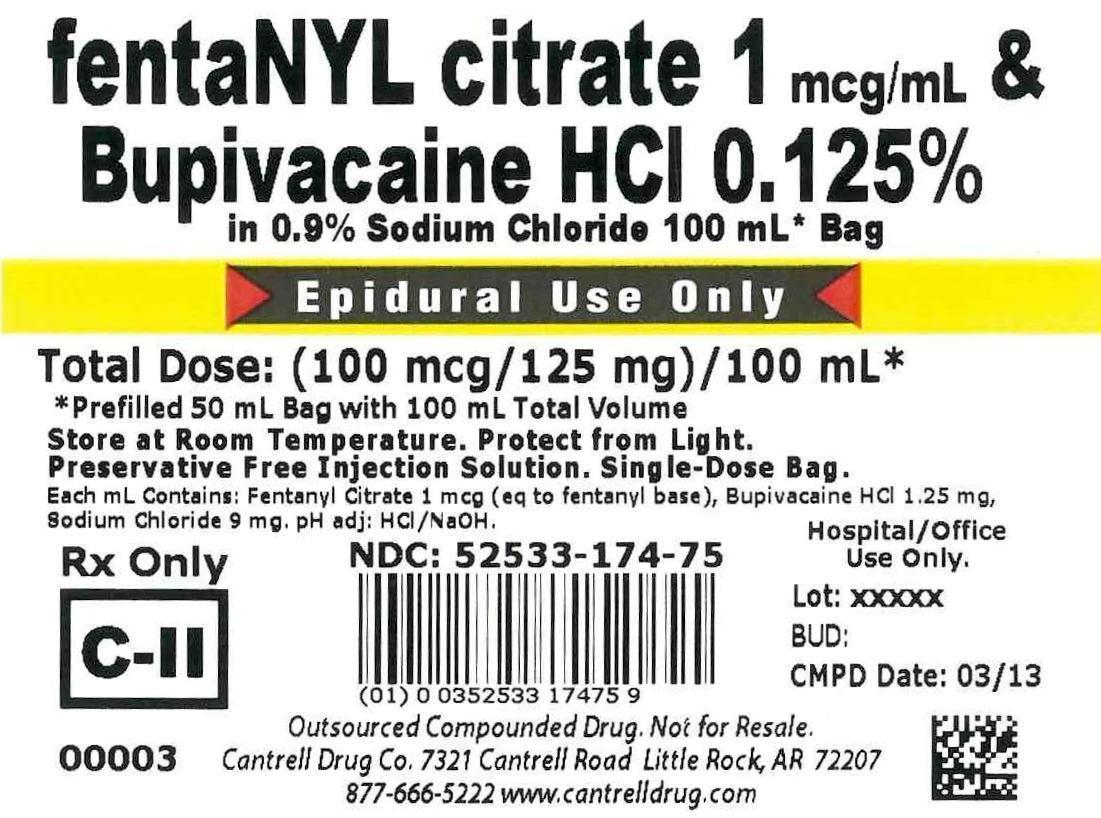 DRUG LABEL: Fentanyl Citrate, Bupivacaine HCl
NDC: 52533-174 | Form: INJECTION, SOLUTION
Manufacturer: Cantrell Drug Company
Category: prescription | Type: HUMAN PRESCRIPTION DRUG LABEL
Date: 20150112
DEA Schedule: CII

ACTIVE INGREDIENTS: FENTANYL CITRATE 1 ug/1 mL; BUPIVACAINE HYDROCHLORIDE 1.25 mg/1 mL
INACTIVE INGREDIENTS: Sodium Chloride 9 mg/1 mL; Water

Fentanyl Citrate 1 mcg/mL & Bupivacaine HCl 0.125% in 0.9% Sodium Chloride 100 mL Bag